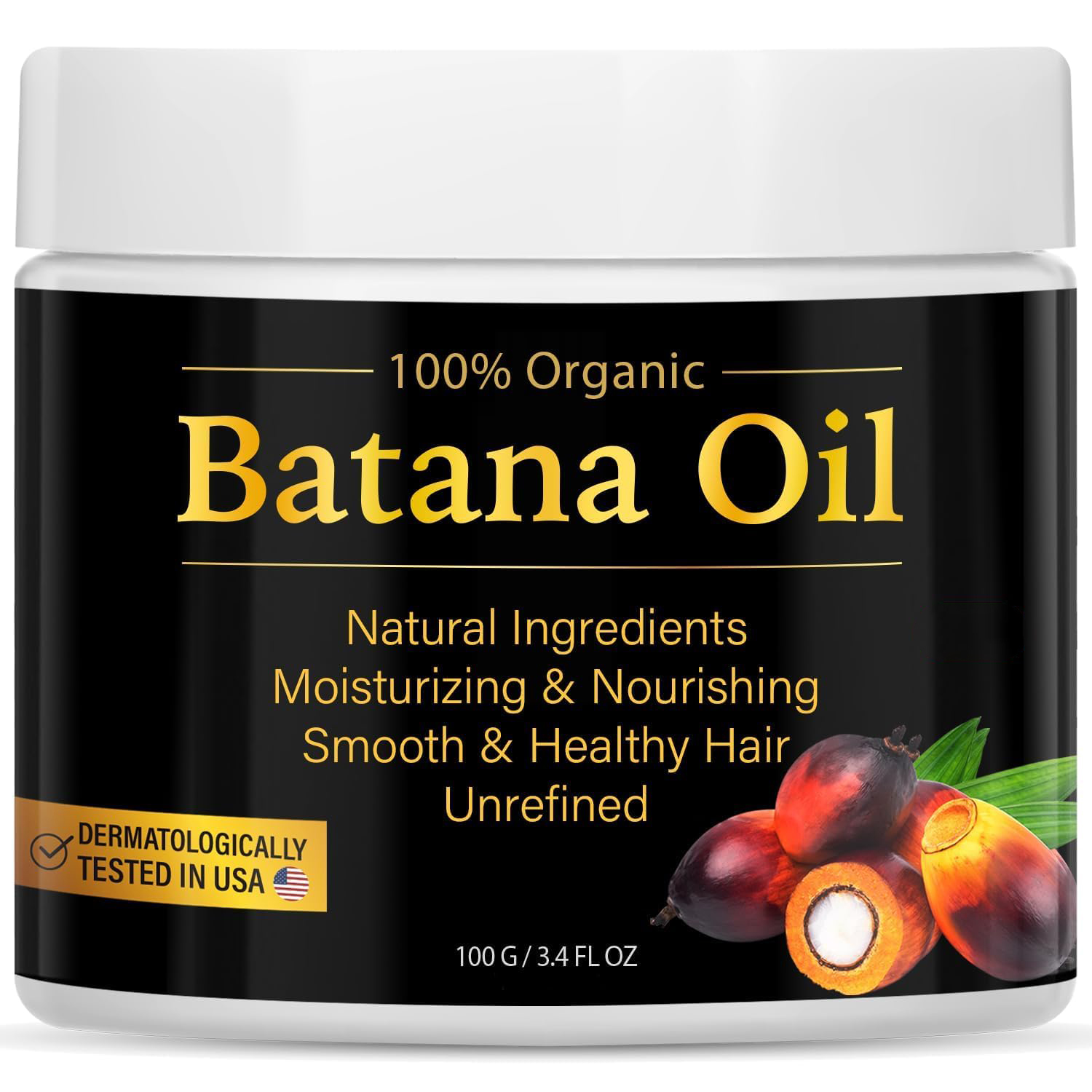 DRUG LABEL: SY Batana Hair Oil
NDC: 84778-031 | Form: CREAM
Manufacturer: Guangzhou Yixin Cross-border E-commerce Co., Ltd.
Category: otc | Type: HUMAN OTC DRUG LABEL
Date: 20241108

ACTIVE INGREDIENTS: ELAEIS OLEIFERA SEED OIL 100 g/100 g
INACTIVE INGREDIENTS: WATER

COMPONENTS

Elaeis Oleifera Kernel Oil

PURPOSE

Used to promote hair growth, nourish and repair damaged hair, and enhance hair strength

INDICATIONS AND USAGE

Take an appropriate amount of SY Batana Hair Oil and apply it on wet hair and scalp. Use your fingertips to gently massage and evenly distribute it. Wait for 15-30 minutes and then wash it off with warm water. You can also use it overnight and wash your hair the next day.

WARNINGS

For external use only.

If sensitive irritation occurs, please stop using and store in a cool and dry place.

DOSAGE AND ADMINISTRATION

For external use only.

DO NOT USE

Scalp wounds or infections, known allergies, severe scalp disorders, those taking medications, pregnant or breastfeeding, oily or acne-prone scalp, and those who experience discomfort during use

WHEN USING

When using, take an appropriate amount of oil and drop it on your palm, then apply it evenly on your scalp. Use your fingertips to gently apply the remaining oil to the ends of your hair, especially the ends of your hair. If your hair is dry, damaged, or needs deep nourishment, use it 2-3 times a week.

Do not use on open wounds or allergic skin.

KEEP OUT OF REACH OF CHILDREN

If sxralowed, get medical help or contact a Poison Conirol Cenler ngiht away.

INACTIVE INGREDIENT

water